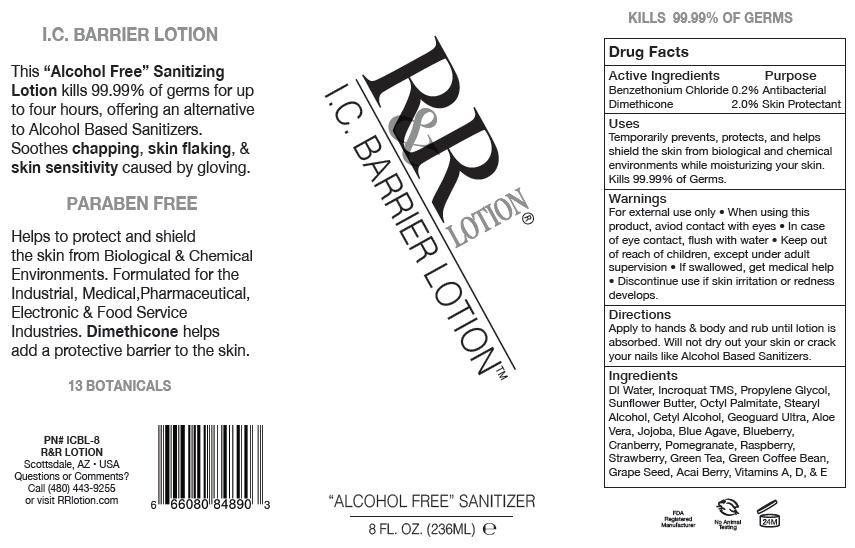 DRUG LABEL: I.C. Barrier
NDC: 59555-601 | Form: LOTION/SHAMPOO
Manufacturer: R&R Lotion, Inc.
Category: otc | Type: HUMAN OTC DRUG LABEL
Date: 20140917

ACTIVE INGREDIENTS: Benzethonium Chloride 2 mg/1 mL; Dimethicone 20 mg/1 mL
INACTIVE INGREDIENTS: Water; Propylene Glycol; Stearyl Alcohol; cholecalciferol; Cetyl Alcohol; vitamin A; .Alpha.-Tocopherol; Ethylhexyl Palmitate

I.C. Barrier Lotion™

Drug Facts

ACTIVE INGREDIENT

Active Ingredients | Purpose
Benzethonium Chloride 0.2% | Antibacterial
Dimethicone 2.0% | Skin Protectant

Uses

Temporarily prevents, protects, and helps shield the skin from biological and chemical environments while moisturizing your skin. Kills 99.99% of Germs.

Warnings

For external use only

- When using this product, aviod contact with eyes
- In case of eye contact, flush with water

- Keep out of reach of children, except under adult supervision
- If swallowed, get medical help
- Discontinue use if skin irritation or redness develops.

Directions

Apply to hands & body and rub until lotion is absorbed. Will not dry out your skin or crack your nails like Alcohol Based Sanitizers.

Ingredients

DI Water, Incroquat TMS, Propylene Glycol, Sunflower Butter, Octyl Palmitate, Stearyl Alcohol, Cetyl Alcohol, Geoguard Ultra, Aloe Vera, Jojoba, Blue Agave, Blueberry, Cranberry, Pomegranate, Raspberry, Strawberry, Green Tea, Green Coffee Bean, Grape Seed, Acai Berry, Vitamins A, D, & E

Questions or Comments?

Call (480) 443-9255 or visit RRlotion.com

PRINCIPAL DISPLAY PANEL - 236 mL Bottle Label

R&R
LOTION®

I.C. BARRIER LOTION™

"ALCOHOL FREE" SANITIZER

8 FL. OZ. (236ML) e